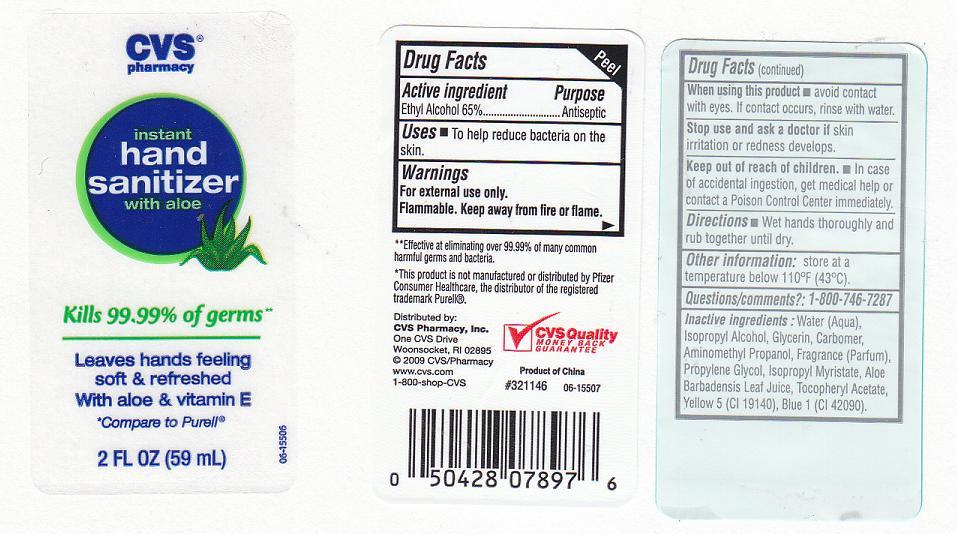 DRUG LABEL: INSTANT HAND SANITIZER
NDC: 59779-254 | Form: GEL
Manufacturer: CVS PHARMACY
Category: otc | Type: HUMAN OTC DRUG LABEL
Date: 20110823

ACTIVE INGREDIENTS: ALCOHOL 65 mL/100 mL
INACTIVE INGREDIENTS: WATER; GLYCERIN; ISOPROPYL MYRISTATE; CARBOMER 934; AMINOMETHYLPROPANOL; PROPYLENE GLYCOL; ALPHA-TOCOPHEROL ACETATE; ALOE VERA LEAF; FD&C BLUE NO. 1; FD&C YELLOW NO. 5; ISOPROPYL ALCOHOL

DRUG FACTS

ACTIVE INGREDIENT

ETHYL ALCOHOL 65%

PURPOSE

ANTISEPTIC

USES

TO HELP REDUCE BACTERIA ON THE SKIN.

WARNINGS

FOR EXTERNAL USE ONLY. FLAMMABLE, KEEP AWAY FROM FIRE OR FLAME.

WHEN USING THIS PRODUCT

AVOID CONTACT WITH EYES. IF CONTACT OCCURS, RINSE WITH WATER.

STOP USING THIS PRODUCT AND ASK DOCTOR IF

IRRITATION OR REDNESS DEVELOPS.

KEEP OUT OF REACH OF CHILDREN

IN CASE OF ACCIDENTAL INGESTION, GET MEDICAL HELP OR CONTACT A POISON CONTROL CENTER IMMEDIATELY.

DIRECTIONS

WET HANDS THOROUGHLY AND RUB TOGETHER UNTIL DRY.

OTHER INFORMATION

STORE AT A TEMPERATURE BELOW 110 DEGREES FAHRENHEIT (43 DEGREES CELSIUS).

QUESTIONS AND COMMENTS

1-800-746-7287

INACTIVE INGREDIENTS

WATER, ISOPROPYL ALCOHOL, GLYCERIN, CARBOMER, AMINOMETHYL PROPANOL, FRAGRANCE, PROPYLENE GLYCOL, ISOPROPYL MYRISTATE, ALOE BARBADENSIS LEAF JUICE, TOCOPHERYL ACETATE, YELLOW 5 (CI 19140), BLUE 1 (CI 42090).